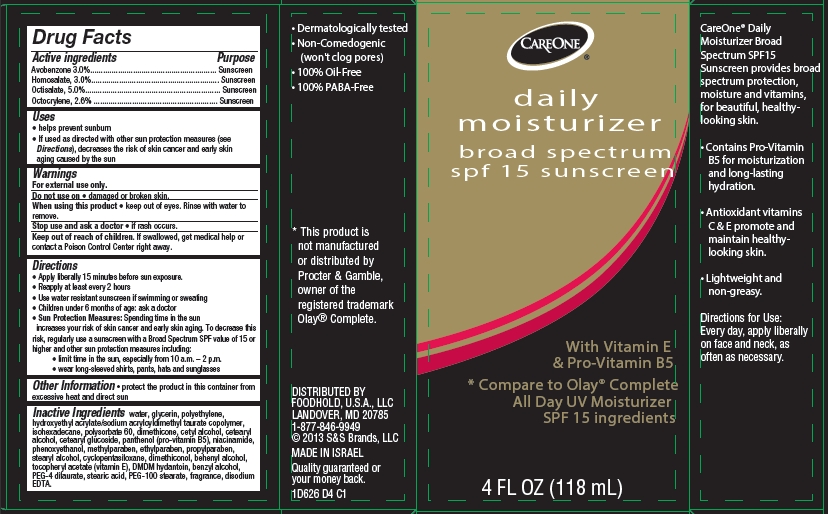 DRUG LABEL: CareOne Daily Moisturizer Broad Spectrum SPF15 Sunscreen
NDC: 41520-626 | Form: LOTION
Manufacturer: American Sales Company
Category: otc | Type: HUMAN OTC DRUG LABEL
Date: 20130930

ACTIVE INGREDIENTS: AVOBENZONE 3 g/100 mL; HOMOSALATE 3 g/100 mL; OCTINOXATE 5 g/100 mL; OCTOCRYLENE 2.6 g/100 mL
INACTIVE INGREDIENTS: WATER; GLYCERIN; HIGH DENSITY POLYETHYLENE; HYDROXYETHYL ACRYLATE/SODIUM ACRYLOYLDIMETHYL TAURATE COPOLYMER (45000 MPA.S AT 1%); ISOHEXADECANE; POLYSORBATE 60; DIMETHICONE; CETYL ALCOHOL; CETOSTEARYL ALCOHOL; CETEARYL GLUCOSIDE; PANTHENOL; NIACINAMIDE; PHENOXYETHANOL; METHYLPARABEN; ETHYLPARABEN; PROPYLPARABEN; STEARYL ALCOHOL; CYCLOMETHICONE 5; DIMETHICONOL (100000 CST); DOCOSANOL; .ALPHA.-TOCOPHEROL ACETATE; DMDM HYDANTOIN; BENZYL ALCOHOL; PEG-4 DILAURATE; PEG-100 STEARATE; STEARIC ACID; EDETATE DISODIUM

CareOne Daily Moisturizer Broad Spectrum SPF15 Sunscreen

Active ingredient

Avobenzone 3.0%

Homosalate 3.0%

Octisalate 5.0%

Octocrylene 2.6%

Purpose

Sunscreen

Uses

- helps prevent sunburn
- If used as directed with other sun protection measures (see Directions), decreases the risk of skin cancer and early skin aging caused by the sun

Warnings

For external use only.

Do not use on

- damaged or broken skin.

When using this product

- keep out of eyes. Rinse with water to remove.

Stop use and ask a doctor

- if rash occurs.

Keep Out of Reach of Children.

If swallowed, get medical help or contact a Poison Control Center right away.

Directions

- Apply liberally 15 minutes before sun exposure.
- Reapply at least every 2 hours
- Use a water resistant sunscreen if swimming or sweating
- Children under 6 months of age: ask a doctor
- Sun Protection Measures: Spending time in the sun increases your risk of skin cancer and early skin aging. To decrease this risk, regularly use a sunscreen with a Broad Spectrum SPF value of 15 or higher and other sun protection measures including:
  - limit time in the sun, especially from 10 a.m. - 2 p.m.
  - wear long-sleeved shirts, pants, hats and sunglasses

Other Information

- protect the product in this container from excessive heat and direct sun

Inactive Ingredients

water, glycerin, polyethylene, hydroxyethyl acrylate/sodium acryloyldimethyl taurate copolymer, isohexadecane, polysorbate 60, dimethicone, cetyl alcohol, cetearyl alcohol, cetearyl glucoside, panthenol (pro-vitamin B5), niacinamide, phenoxyethanol, methylparaben, ethylparaben, propylparaben, stearyl alcohol, cyclopentasiloxane, dimethiconol, behenyl alcohol, tocopheryl acetate (vitamin E), DMDM hydantoin, benzyl alcohol, PEG-4 dilaurate, stearic acid, PEG-100 stearate, fragrance, disodium EDTA

Package/Label Principal Display Panel

CareOne® Daily Moisturizer

broad spectrum SPF15 sunscreen

With Vitamin E & Pro-Vitamin B5

*Compare to Olay® Complete
All Day UV Moisturizer SPF 15
Ingredients

- Dermatologically tested
- Non-Comedogenic (won't clog pores)
- 100% Oil-Free
- 100% PABA-Free

4 FL OZ (118 mL)

*This product is not made or distributed by Procter & Gamble, owner of the registered trademark Olay® Complete.

CareOne® Daily Moisturizer Broad Spectrum SPF15 Sunscreen provides broad spectrum protection, moisture and vitamins, for beautiful, healthy-looking skin.

- Contains Pro-Vitamin B5 for moisturization and long-lasting hydration.
- Antioxidant vitamins C & E promote and maintain healthy-looking skin.
- Lightweight and non-greasy.

Directions for Use:
Every day, apply liberally on face and neck, as often as necessary.

DISTRIBUTED BY FOODHOLD, U.S.A., LLC
LANDOVER, MD 20785
1-877-846-9949
© 2013 S&S Brands, LLC

MADE IN ISRAEL

Quality guaranteed or your money back.
1D626 D4 C1

Carton Label